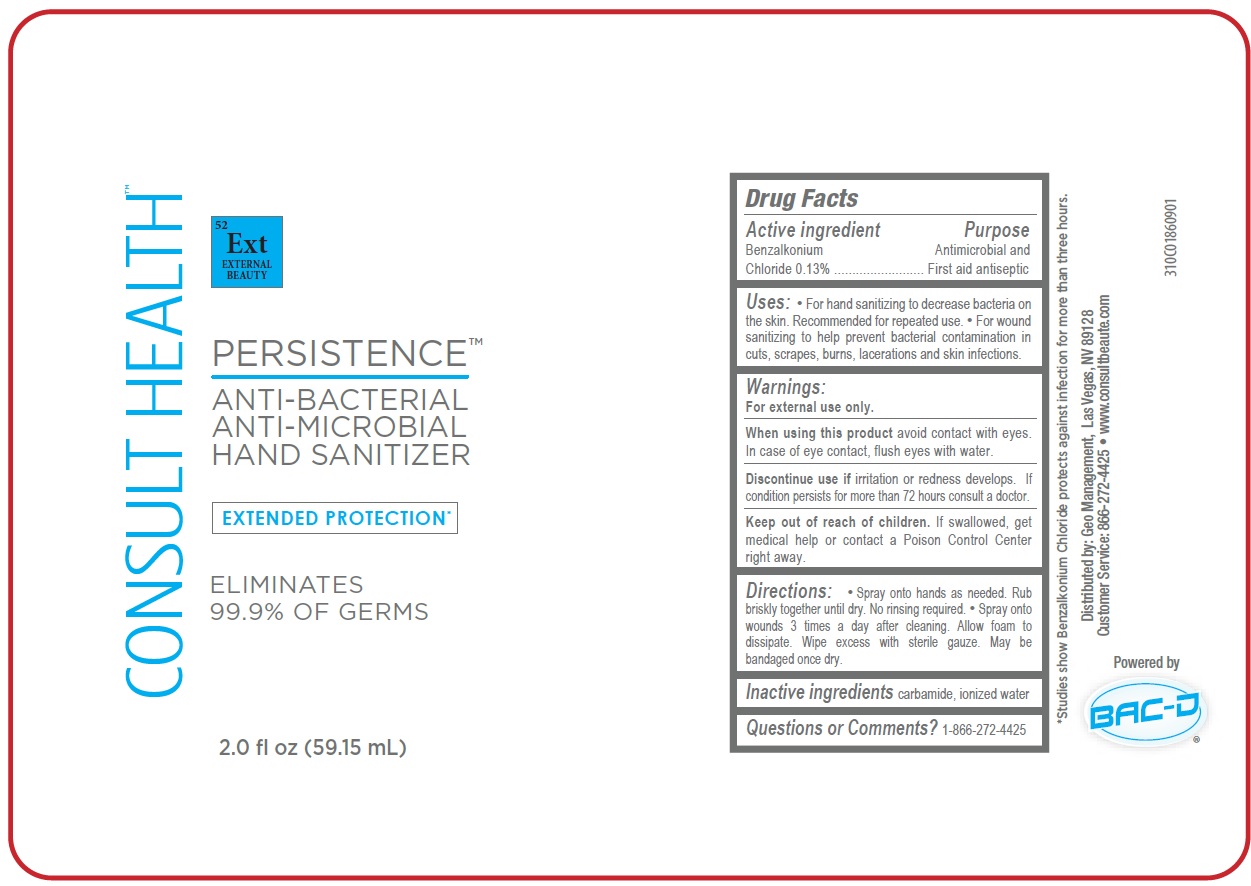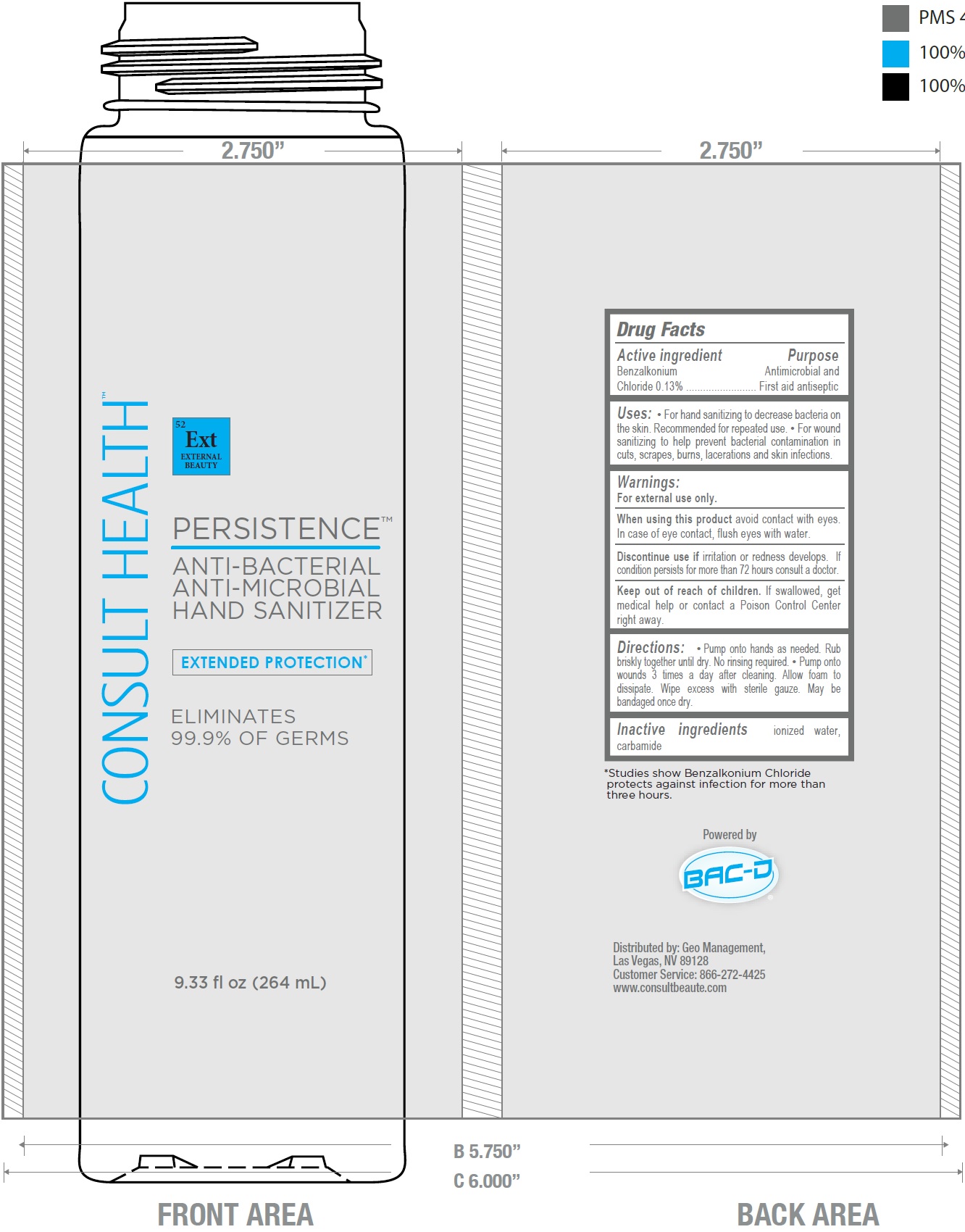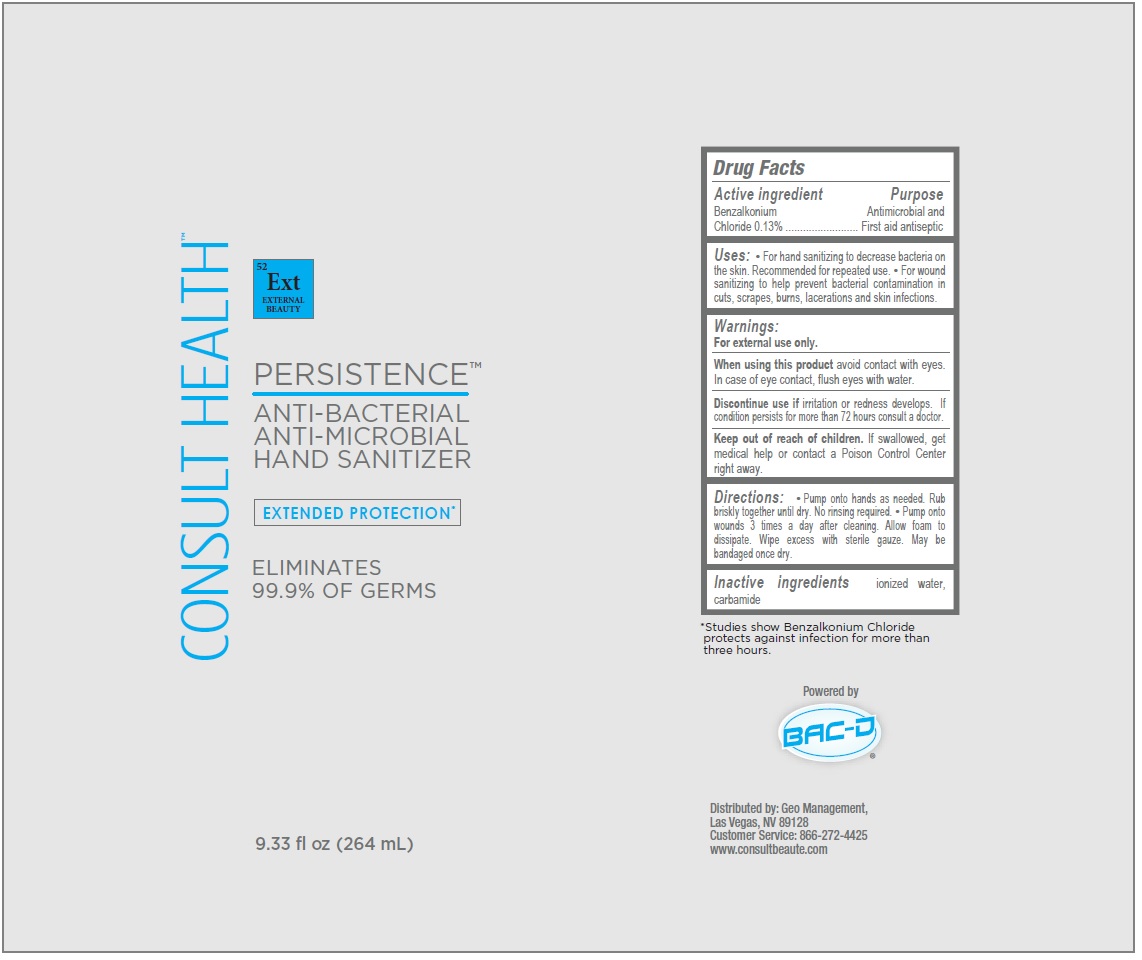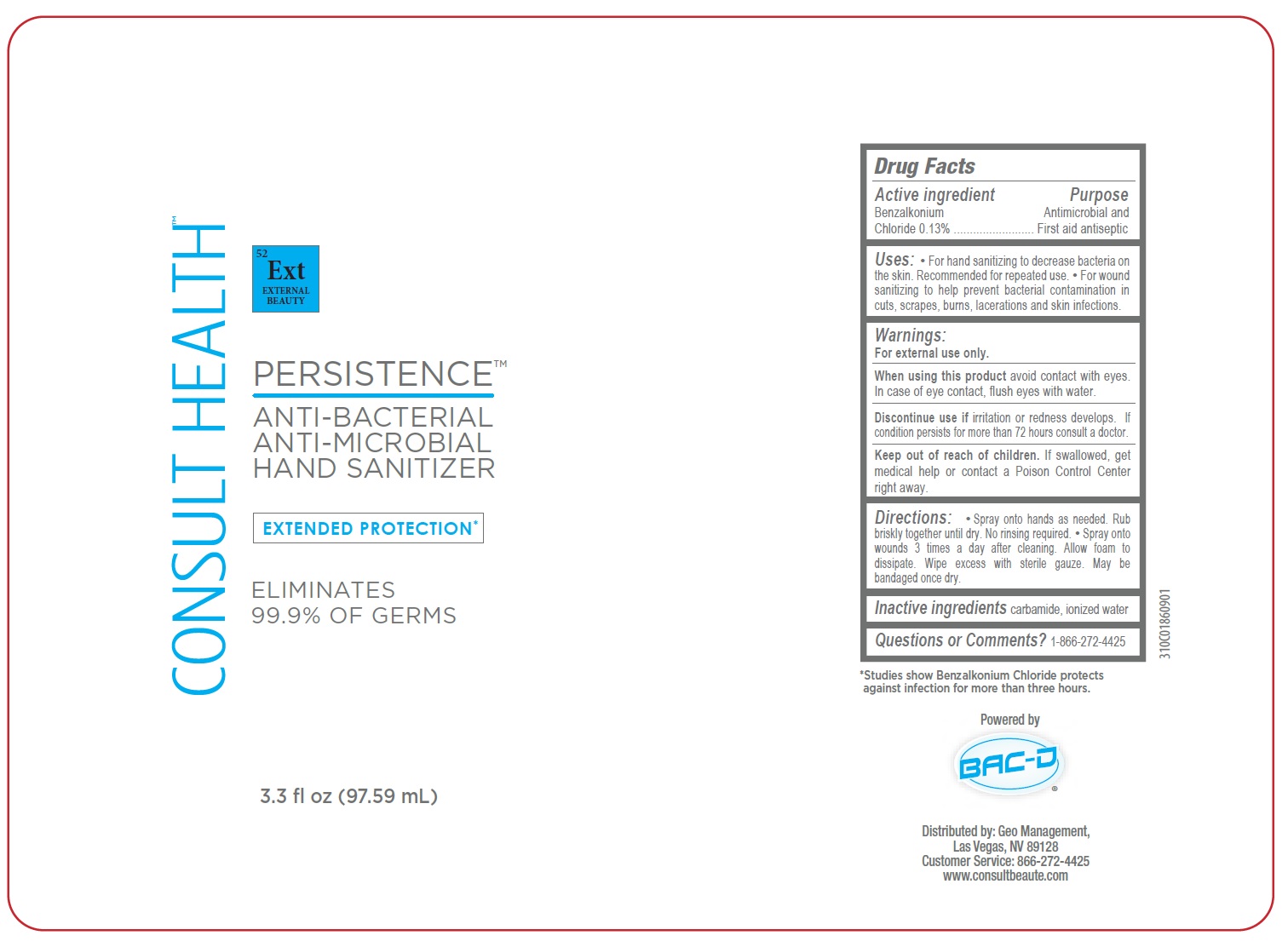 DRUG LABEL: Consult Health Persistence Hand Sanitizer
NDC: 70803-004 | Form: LIQUID
Manufacturer: Geo Management Corporation
Category: otc | Type: HUMAN OTC DRUG LABEL
Date: 20210723

ACTIVE INGREDIENTS: BENZALKONIUM CHLORIDE 1.3 mg/1 mL
INACTIVE INGREDIENTS: WATER; UREA

Consult Health Persistence Hand Sanitizer

Active ingredient

Benzalkonium Chloride 0.13%

Purpose

Antimicrobial and First aid antiseptic

Uses:

• For hand sanitizing to decrease bacteria on the skin. Recommended for repeated use. • For wound sanitizing to help prevent bacterial contamination in cuts, scrapes, burns, lacerations and skin infections.

Warnings:

For external use only.

When using this product

avoid contact with eyes. In case of eye contact, flush eyes with water.

Discontinue use if

irritation or redness develops. If condition persists for more than 72 hours consult a doctor.

Keep out of reach of children.

If swallowed, get medical help or contact a Poison Control Center right away.

Directions:

• Spray onto hands as needed. Pump onto hands as needed. Rub briskly together until dry. No rinsing required. • Pump onto wounds 3 times a day after cleaning. Allow foam to dissipate. Wipe excess with sterile gauze. May be bandaged once dry.

Inactive ingredients

ionized water, carbamide

Questions or Comments?

1-866-272-4425